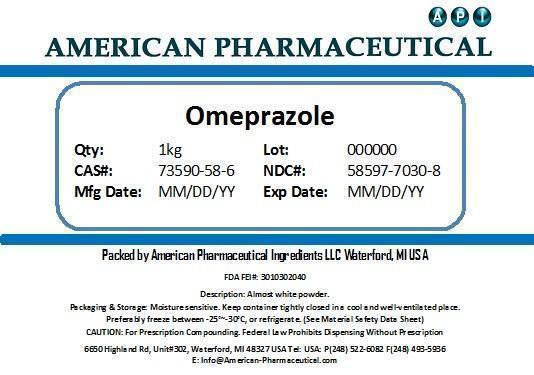 DRUG LABEL: Omeprazole
NDC: 58597-7030 | Form: POWDER
Manufacturer: AMERICAN PHARMACEUTICAL INGREDIENTS LLC
Category: other | Type: BULK INGREDIENT
Date: 20130812

ACTIVE INGREDIENTS: OMEPRAZOLE 1 g/1 g

Omeprazole